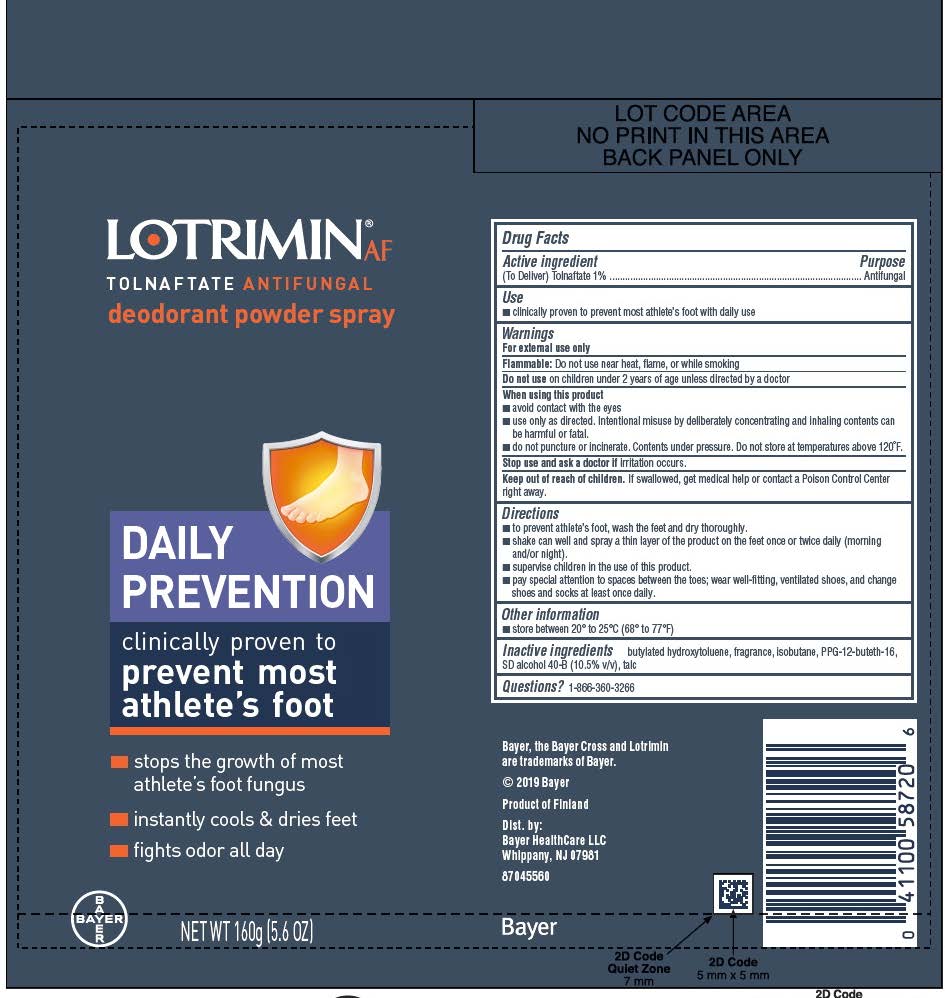 DRUG LABEL: Lotrimin Daily Prevention Deo
NDC: 11523-0010 | Form: AEROSOL, POWDER
Manufacturer: Bayer HealthCare LLC.
Category: otc | Type: HUMAN OTC DRUG LABEL
Date: 20251204

ACTIVE INGREDIENTS: TOLNAFTATE 10 mg/1 g
INACTIVE INGREDIENTS: ALCOHOL; TALC; BUTYLATED HYDROXYTOLUENE; PPG-12-BUTETH-16; ISOBUTANE

Lotrimin Daily Prevention Deo Powder Spray UI 1612507

Drug Facts

Active Ingredient

(To Deliver)Tolnaftate 1%

Purpose

Antifungal

Use

clinically proven to prevent most athlete’s foot with daily use

Warnings

For external use only

Flammable: Do not use near heat, flame, or while smoking

Do not use on children under 2 years of age unless directed by a doctor

Stop use and ask a doctor if irritation occurs.

Keep out of reach of children. If swallowed, get medical help or contact a Poison Control Center right away.

When using this product

avoid contact with the eyes
use only as directed. Intentional misuse by deliberately concentrating and inhaling contents can be harmful or fatal.
do not puncture or incinerate. Contents under pressure. Do not store at temperatures above 120ºF

Directions

to prevent athlete’s foot, wash the feet and dry thoroughly.
shake can well and spray a thin layer of the product on the feet once or twice daily (morning and/or night)
supervise children in the use of this product.
pay special attention to spaces between the toes; wear well-fitting, ventilated shoes, and change shoes and socks at least once daily.

Other information

store between 20º to 25ºC (68º– 77ºF)

Inactive Ingredients

butylated hydroxytoluene, fragrance, isobutane, PEG-12-Buteth-16, SD alcohol 40B (10.5% v/v), talc

Questions? 1-866-360-3266

Display can 160 grams

Lotrimin®AF

TOLNAFTATE ANTIFUNGAL

deodorant powder spray

DAILY PREVENTION

clinically proven to

prevent most

athlete's foot

- stops the growth of most athlete's foot fungus
- instantly cools and dries feet
- fights odor all day

NET WT 160 g (5.6 OZ)